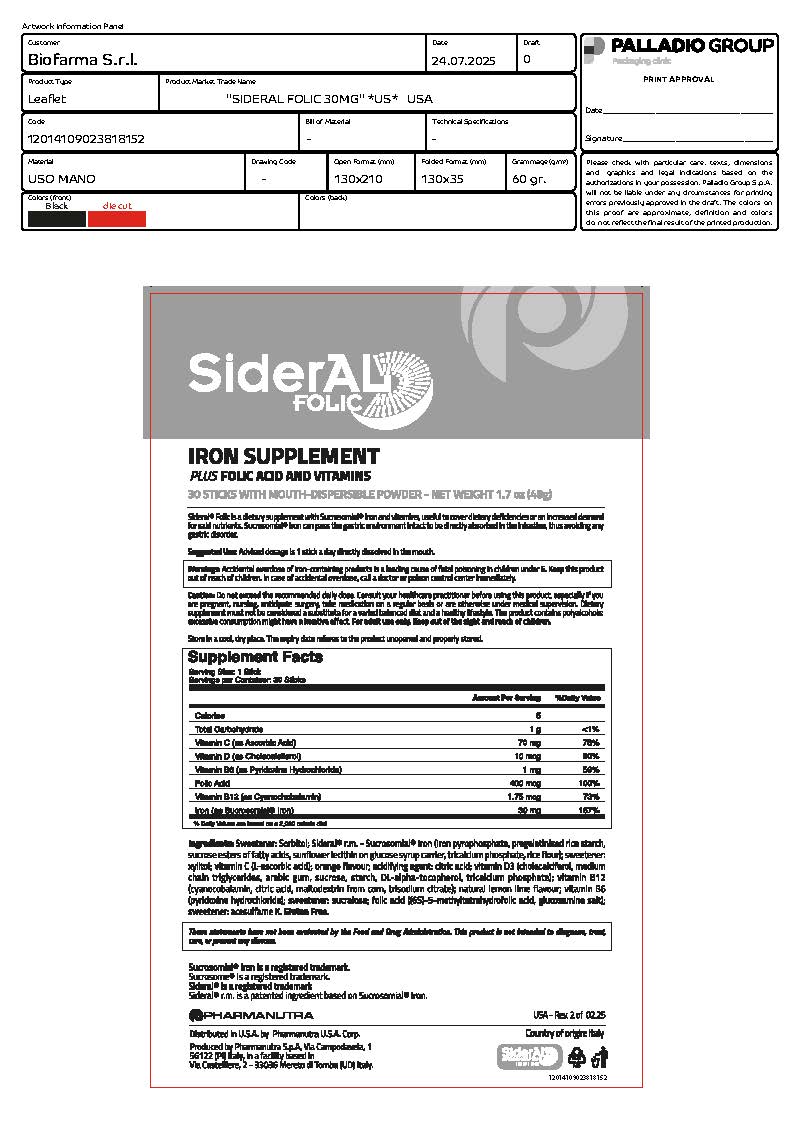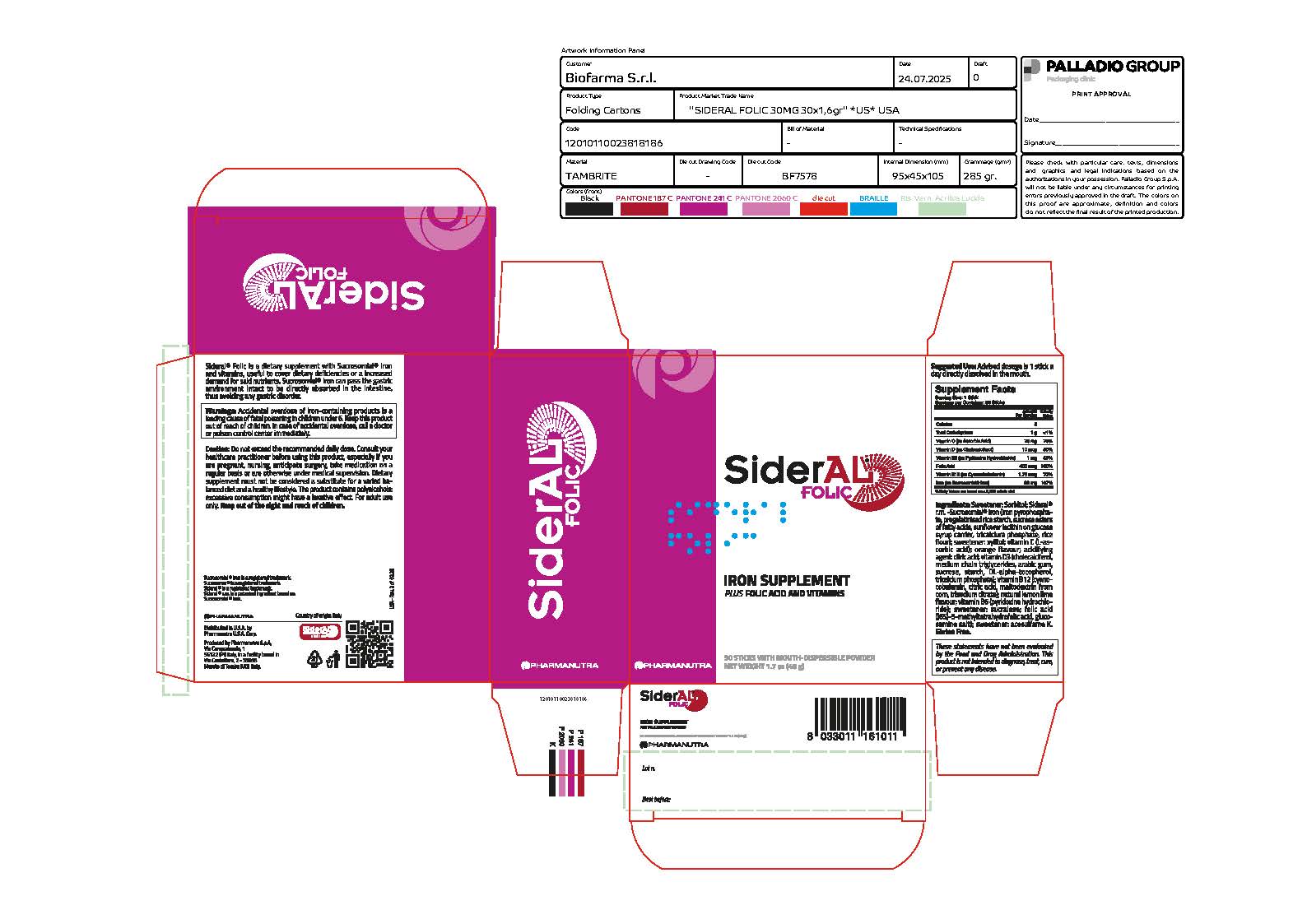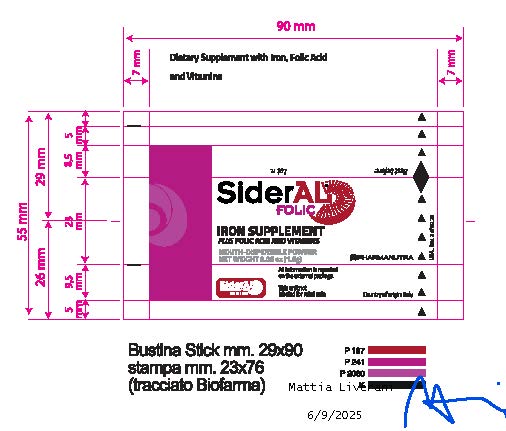 DRUG LABEL: SiderAL Folic
NDC: 84797-002 | Form: POWDER
Manufacturer: PharmaNutra Usa Corp.
Category: other | Type: Dietary Supplement
Date: 20250814

ACTIVE INGREDIENTS: IRON 30 mg/1 mg; ASCORBIC ACID 70 mg/1 mg; CHOLECALCIFEROL 0.01 mg/1 mg; PYRIDOXINE HYDROCHLORIDE 1 mg/1 mg; FOLIC ACID .4 mg/1 mg; CYANOCOBALAMIN 0.00175 mg/1 mg
INACTIVE INGREDIENTS: SORBITOL; ACESULFAME POTASSIUM; SUCRALOSE; XYLITOL; CITRIC ACID

SiderAL Folic
Plus Folic Acid adn Vitamins

STATEMENT OF IDENTITY

Supplement Facts
Serving Size: 1 Stick
Serving per container: 30 sticks
Amount per Serving % Daily Value

Calories 5

Total Carbohydrate 1 g <1%

Vitamin C (as Ascorbic Acid) 70 mg 78%

Vitamin D (as Cholecalciferol) 10 mcg 50%

Vitamin B6 (as Pyridoxine Hydrochloride) 1 mg 59%

Folic Acid 400 mcg 100%

Vitamin B12 (as Cyanochobalamin) 1.75 mcg 73%

Iron (as Iron Pyrophosphate) 30 mg 167%

DOSAGE AND ADMINISTRATION

Suggested use: Advised dosage is 1 stick a day directly dissolved in the mouth.

HEALTH CLAIM

Sideal Folic is a dietary supplement with Sucrosomial Iron and vitamins, useful to cover dietary deficiencies or a increased demand for said nutrients. Sucrosomial Iron can pass the gastric environment intact to be directly absorbed in the intestine, thus avoiding any gastric disorder.

WARNINGS

Warnings: Accidental overdose of iron containing products is a leading cause of fatal poisoning in children under 6. Keep this product out of reach of children.In case of accidental overdose, call a doctor or poison control center immediately.

PRECAUTIONS

Caution: Do not exceed the recommended daily dose. Consult your healthcare practitioner before using this product, especially if you are pregnant, nursing, anticipate surgery, take medication on a regular basis or are otherwise under medical supervision. Dietary supplement must not be considered a substitute for a varied balanced diet and a healthy lifestyle. The product contains polyalcohols; excessive consumption might have a laxative effect. For adult use only. Keep out of the sight and reach of children.